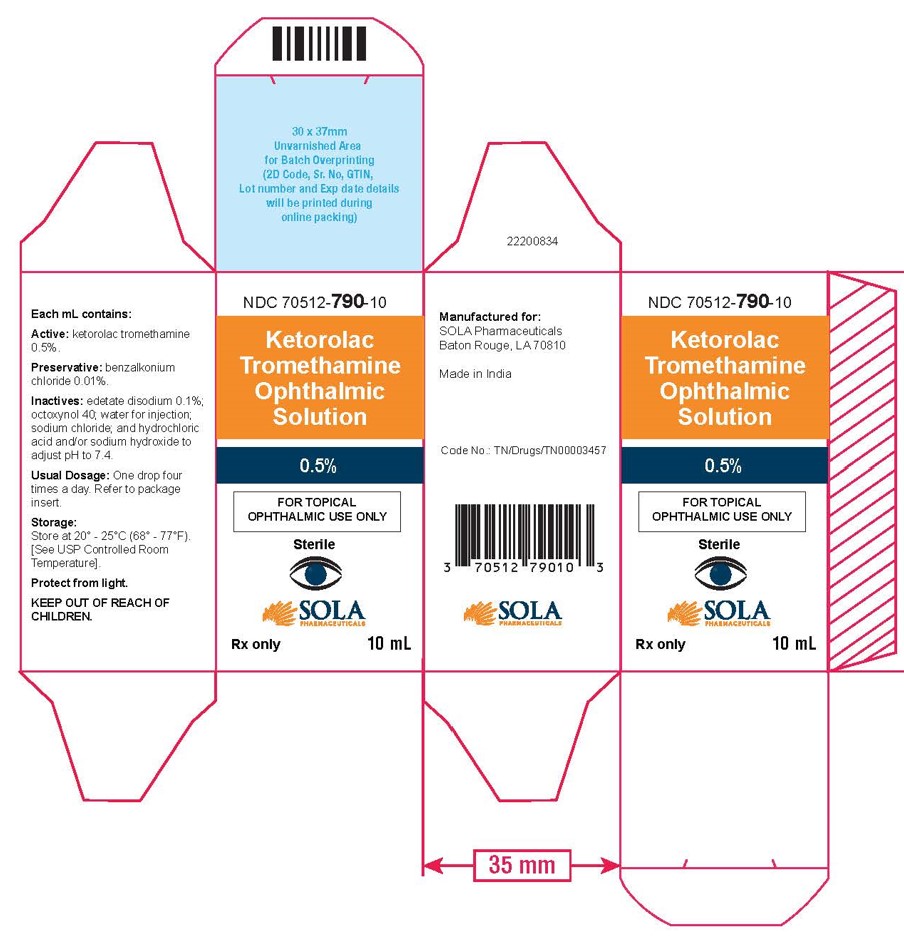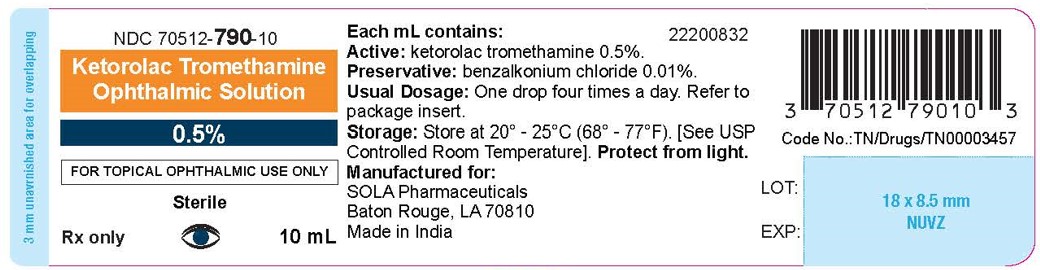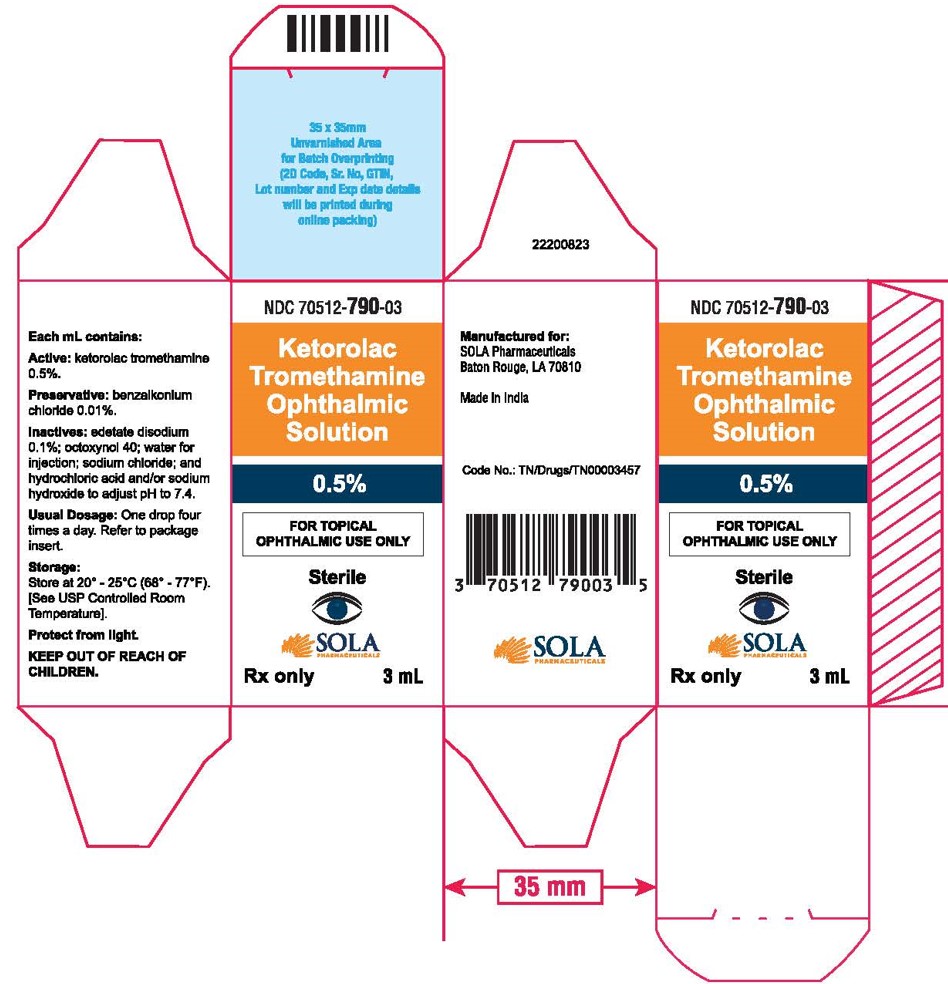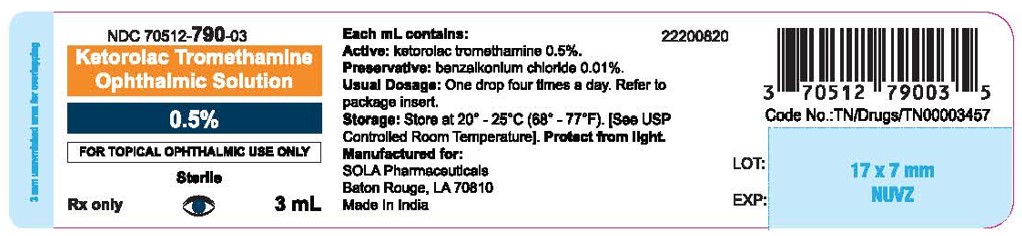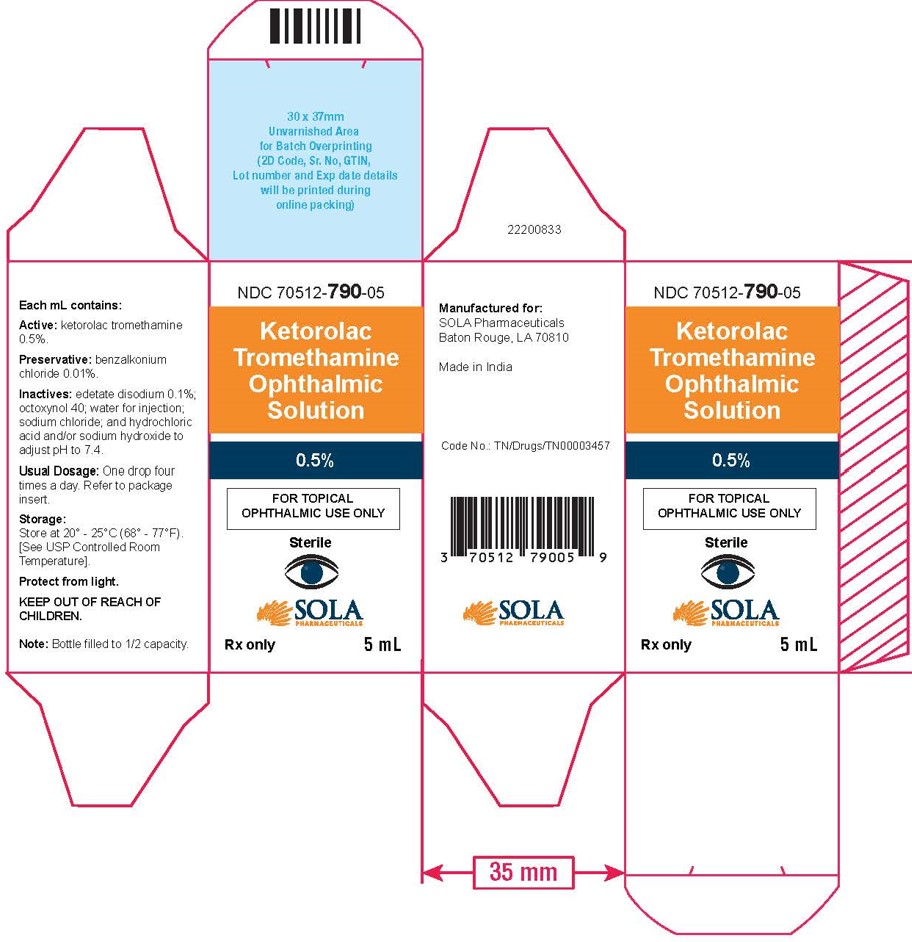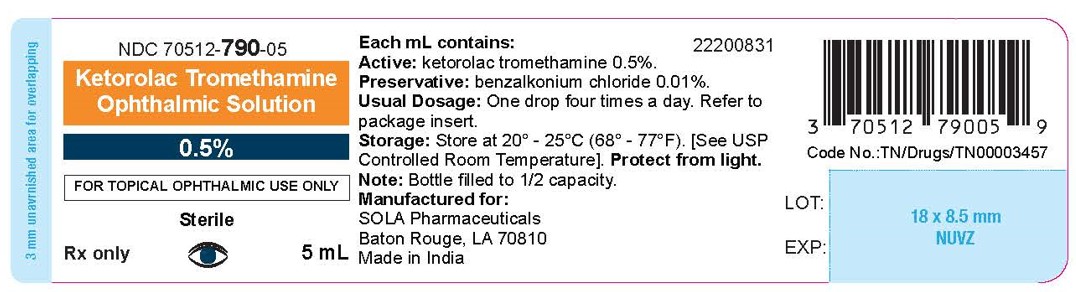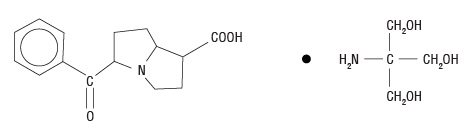 DRUG LABEL: Ketorolac Tromethamine
NDC: 67296-2210 | Form: SOLUTION
Manufacturer: Redpharm Drug
Category: prescription | Type: HUMAN PRESCRIPTION DRUG LABEL
Date: 20260131

ACTIVE INGREDIENTS: KETOROLAC TROMETHAMINE 5 mg/1 mL
INACTIVE INGREDIENTS: BENZALKONIUM CHLORIDE; EDETATE DISODIUM; OCTOXYNOL-40; SODIUM CHLORIDE; HYDROCHLORIC ACID; SODIUM HYDROXIDE; WATER

HIGHLIGHTS OF PRESCRIBING INFORMATION

These highlights do not include all the information needed to use KETOROLAC TROMETHAMINE OPHTHALMIC SOLUTION safely and effectively. See full prescribing information for KETOROLAC TROMETHAMINE OPHTHALMIC SOLUTION.
KETOROLAC TROMETHAMINE ophthalmic solution, 0.5%
Initial U.S. Approval: 1991

1 INDICATIONS AND USAGE

Ketorolac tromethamine ophthalmic solution is a nonsteroidal, anti-inflammatory indicated for:

- The treatment of inflammation following cataract surgery. (1)
- The temporary relief of ocular itching due to seasonal allergic conjunctivitis. (1)

2 DOSAGE AND ADMINISTRATION

One drop of ketorolac tromethamine ophthalmic solution should be applied to the affected eye(s) four times a day for relief of ocular itching due to seasonal allergic conjunctivitis.

For the treatment of postoperative inflammation in patients who have undergone cataract extraction, one drop of ketorolac tromethamine ophthalmic solution should be applied to the affected eye four times daily beginning 24 hours after cataract surgery and continuing through the first 2 weeks of the postoperative period. (2.1)

3 DOSAGE FORMS AND STRENGTHS

Ophthalmic solution containing 5 mg/mL ketorolac tromethamine. (3)

- 5 mL size bottle filled with 3 mL of solution
- 10 mL size bottle filled with 5 mL of solution
- 10 mL size bottle filled with 10 mL of solution

4 CONTRAINDICATIONS

Hypersensitivity to any component of this product. (4)

5 WARNINGS AND PRECAUTIONS

- Delayed healing (5.1)
- Cross-sensitivity or hypersensitivity (5.2)
- Increased bleeding time due to interference with thrombocyte aggregation (5.3)
- Corneal effects including keratitis (5.4)

6 ADVERSE REACTIONS

The most frequent adverse reactions reported by up to 40% of patients participating in clinical trials have been transient stinging and burning on instillation. (6.1)

To report SUSPECTED ADVERSE REACTIONS, contact SOLA Pharmaceuticals at 1-866-747-7365 or FDA at 1-800-FDA-1088 orwww.fda.gov/medwatch.

FULL PRESCRIBING INFORMATION

1 INDICATIONS AND USAGE

Ketorolac tromethamine ophthalmic solution is indicated for the temporary relief of ocular itching due to seasonal allergic conjunctivitis. Ketorolac tromethamine ophthalmic solution is also indicated for the treatment of postoperative inflammation in patients who have undergone cataract extraction.

2 DOSAGE AND ADMINISTRATION

2.1 Recommended Dosing

Patient Dosing

The recommended dose of ketorolac tromethamine ophthalmic solution is one drop four times a day to the affected eye(s) for relief of ocular itching due to seasonal allergic conjunctivitis.

For the treatment of postoperative inflammation in patients who have undergone cataract extraction, one drop of ketorolac tromethamine ophthalmic solution should be applied to the affected eye four times daily beginning 24 hours after cataract surgery and continuing through the first 2 weeks of the postoperative period.

2.2 Use with Other Topical Ophthalmic Medications

Ketorolac tromethamine ophthalmic solution has been safely administered in conjunction with other ophthalmic medications such as antibiotics, alpha-agonists, beta blockers, carbonic anhydrase inhibitors, cycloplegics, and mydriatics. Drops should be administered at least 5 minutes apart.

3 DOSAGE FORMS AND STRENGTHS

5 mL size bottle filled with 3 mL of ketorolac tromethamine ophthalmic solution, 0.5% (5 mg/mL)
10 mL size bottle filled with 5 mL of ketorolac tromethamine ophthalmic solution, 0.5% (5 mg/mL)
10 mL size bottle filled with 10 mL of ketorolac tromethamine ophthalmic solution, 0.5% (5 mg/mL)

4 CONTRAINDICATIONS

Ketorolac tromethamine ophthalmic solution is contraindicated in patients with previously demonstrated hypersensitivity to any of the ingredients in the formulation.

5 WARNINGS AND PRECAUTIONS

5.1 Delayed Healing

Topical nonsteroidal anti-inflammatory drugs (NSAIDs) may slow or delay healing. Topical corticosteroids are also known to slow or delay healing. Concomitant use of topical NSAIDs and topical steroids may increase the potential for healing problems.

5.2 Cross-Sensitivity or Hypersensitivity

There is the potential for cross-sensitivity to acetylsalicylic acid, phenylacetic acid derivatives, and other NSAIDs. There have been reports of bronchospasm or exacerbation of asthma associated with the use of ketorolac tromethamine ophthalmic solution in patients who have either a known hypersensitivity to aspirin/non-steroidal anti-inflammatory drugs or a past medical history of asthma. Therefore, caution should be used when treating individuals who have previously exhibited sensitivities to these drugs.

5.3 Increased Bleeding Time

With some NSAIDs, there exists the potential for increased bleeding time due to interference with thrombocyte aggregation. There have been reports that ocularly applied nonsteroidal anti-inflammatory drugs may cause increased bleeding of ocular tissues (including hyphemas) in conjunction with ocular surgery.

It is recommended that ketorolac tromethamine ophthalmic solution be used with caution in patients with known bleeding tendencies or who are receiving other medications, which may prolong bleeding time.

5.4 Corneal Effects

Use of topical NSAIDs may result in keratitis. In some susceptible patients, continued use of topical NSAIDs may result in epithelial breakdown, corneal thinning, corneal erosion, corneal ulceration, or corneal perforation. These events may be sight threatening. Patients with evidence of corneal epithelial breakdown should immediately discontinue use of topical NSAIDs and should be closely monitored for corneal health.

Postmarketing experience with topical NSAIDs suggests that patients with complicated ocular surgeries, corneal denervation, corneal epithelial defects, diabetes mellitus, ocular surface diseases (e.g., dry eye syndrome), rheumatoid arthritis, or repeat ocular surgeries within a short period of time may be at increased risk for corneal adverse events which may become sight threatening. Topical NSAIDs should be used with caution in these patients.

Postmarketing experience with topical NSAIDs also suggests that use more than 1 day prior to surgery or use beyond 14 days post-surgery may increase patient risk for the occurrence and severity of corneal adverse events.

5.5 Contact Lens Wear

Ketorolac tromethamine ophthalmic solution should not be administered while wearing contact lenses.

6 ADVERSE REACTIONS

6.1 Clinical Studies Experience

Because clinical studies are conducted under widely varying conditions, adverse reaction rates observed in the clinical studies of a drug cannot be directly compared to the rates in the clinical studies of another drug and may not reflect the rates observed in practice.

The most frequent adverse reactions reported with the use of ketorolac tromethamine ophthalmic solutions have been transient stinging and burning on instillation. These reactions were reported by up to 40% of patients participating in clinical trials.

Other adverse reactions occurring approximately 1 to 10% of the time during treatment with ketorolac tromethamine ophthalmic solutions included allergic reactions, corneal edema, iritis, ocular inflammation, ocular irritation, superficial keratitis, and superficial ocular infections.

Other adverse reactions reported rarely with the use of ketorolac tromethamine ophthalmic solutions included: corneal infiltrates, corneal ulcer, eye dryness, headaches, and visual disturbance (blurry vision).

6.2 Postmarketing Experience

The following adverse reactions have been identified during post-marketing use of ketorolac tromethamine ophthalmic solution 0.5% in clinical practice. Because they are reported voluntarily from a population of unknown size, estimates of frequency cannot be made. The reactions, which have been chosen for inclusion due to either their seriousness, frequency of reporting, possible causal connection to topical ketorolac tromethamine ophthalmic solution 0.5% or a combination of these factors, include bronchospasm or exacerbation of asthma, corneal erosion, corneal perforation, corneal thinning, and epithelial breakdown [see Warnings and Precautions (5.2, 5.4)].

8 USE IN SPECIFIC POPULATIONS

8.1 Pregnancy

Teratogenic Effects. Pregnancy Category C

Pregnancy Category C: Ketorolac tromethamine, administered during organogenesis, was not teratogenic in rabbits and rats at oral doses of 3.6 mg/kg/day and 10 mg/kg/day, respectively. These doses are approximately 100 times and 250 times higher respectively than the maximum recommended human topical ophthalmic daily dose of 2 mg (5 mg/ mL x 0.05 mL/drop, x 4 drops x 2 eyes) to affected eyes on a mg/kg basis. Additionally, when administered to rats after Day 17 of gestation at oral doses up to 1.5 mg/kg/day (approximately 40 times the typical human topical ophthalmic daily dose), ketorolac tromethamine resulted in dystocia and increased pup mortality. There are no adequate and well-controlled studies in pregnant women. Ketorolac tromethamine ophthalmic solution should be used during pregnancy only if the potential benefit justifies the potential risk to the fetus.

NONTERATOGENIC EFFECTS

Nonteratogenic Effects:Because of the known effects of prostaglandin-inhibiting drugs on the fetal cardiovascular system (closure of the ductus arteriosus), the use of ketorolac tromethamine ophthalmic solution during late pregnancy should be avoided.

8.3 Nursing Mothers

Because many drugs are excreted in human milk, caution should be exercised when ketorolac tromethamine ophthalmic solution is administered to a nursing woman.

8.4 Pediatric Use

Safety and efficacy in pediatric patients below the age of 2 have not been established.

8.5 Geriatric Use

No overall clinical differences in safety or effectiveness have been observed between elderly and other adult patients.

11 DESCRIPTION

Ketorolac tromethamine ophthalmic solution 0.5% is a member of the pyrrolo-pyrrole group of nonsteroidal anti-inflammatory drugs (NSAIDs) for ophthalmic use. Its chemical name is (±)-5-Benzoyl-2, 3-dihydro-1H pyrrolizine-1-carboxylic acid compound with 2-amino-2-(hydroxymethyl)-1,3-propanediol (1:1) and it has the following structure:

Ketorolac tromethamine ophthalmic solution is supplied as a sterile isotonic aqueous 0.5% solution, with a pH of 7.4. Ketorolac tromethamine ophthalmic solution is a racemic mixture of R-(+) and S-(-) -ketorolac tromethamine. Ketorolac tromethamine may exist in three crystal forms. All forms are equally soluble in water. The pKa of ketorolac is 3.5. This white to off-white crystalline substance discolors on prolonged exposure to light. The molecular weight of ketorolac tromethamine is 376.41. The osmolality of ketorolac tromethamine ophthalmic solution is 290 mOsmol/kg.

Each mL of ketorolac tromethamine ophthalmic solution contains: Active:ketorolac tromethamine 0.5%. Preservative:benzalkonium chloride 0.01%. Inactives:edetate disodium 0.1%; octoxynol 40; water for injection; sodium chloride; hydrochloric acid and/or sodium hydroxide to adjust the pH.

12 CLINICAL PHARMACOLOGY

12.1 Mechanism of Action

Ketorolac tromethamine is a nonsteroidal anti-inflammatory drug which, when administered systemically, has demonstrated analgesic, anti-inflammatory, and anti-pyretic activity. The mechanism of its action is thought to be due to its ability to inhibit prostaglandin biosynthesis

12.3 Pharmacokinetics

Two drops of 0.5% ketorolac tromethamine ophthalmic solution instilled into the eyes of patients 12 hours and 1 hour prior to cataract extraction achieved a mean ketorolac concentration of 95 ng/mL in the aqueous humor of 8 of 9 eyes tested (range 40 to 170 ng/mL).

One drop of 0.5% ketorolac tromethamine ophthalmic solution was instilled into 1 eye and 1 drop of vehicle into the other eye TID in 26 healthy subjects. Five (5) of 26 subjects had detectable concentrations of ketorolac in their plasma (range 11 to 23 ng/mL) at Day 10 during topical ocular treatment. The range of concentrations following TID dosing of 0.5% ketorolac tromethamine ophthalmic solution are approximately 4 to 8% of the steady state mean minimum plasma concentration observed following four times daily oral administration of 10 mg ketorolac in humans (290 ± 70 ng/mL).

13 NONCLINICAL TOXICOLOGY

13.1 Carcinogenesis, Mutagenesis, Impairment of Fertility

Ketorolac tromethamine was not carcinogenic in either rats given up to 5 mg/kg/day orally for 24 months or in mice given 2 mg/kg/day orally for 18 months. These doses are approximately 125 times and 50 times higher respectively than the maximum recommended human topical ophthalmic daily dose given as QID for itching to affected eyes on a mg/kg basis.

Ketorolac tromethamine was not mutagenic in vitroin the Ames assay or in forward mutation assays. Similarly, it did not result in an in vitroincrease in unscheduled DNA synthesis or an in vivoincrease in chromosome breakage in mice. However, ketorolac tromethamine did result in an increased incidence in chromosomal aberrations in Chinese hamster ovary cells. Ketorolac tromethamine did not impair fertility when administered orally to male and female rats at doses up to 9 mg/kg/day and 16 mg/kg/day, respectively. These doses are respectively 225 and 400 times higher than the typical human topical ophthalmic daily dose.

14 CLINICAL STUDIES

Two controlled clinical studies showed that ketorolac tromethamine ophthalmic solution was significantly more effective than its vehicle in relieving ocular itching caused by seasonal allergic conjunctivitis.

Two controlled clinical studies showed that patients treated for two weeks with ketorolac tromethamine ophthalmic solution were less likely to have measurable signs of inflammation (cell and flare) than patients treated with its vehicle.

Results from clinical studies indicate that ketorolac tromethamine has no significant effect upon intraocular pressure; however, changes in intraocular pressure may occur following cataract surgery.

16 HOW SUPPLIED/STORAGE AND HANDLING

Ketorolac tromethamine ophthalmic solution 0.5% is supplied sterile, in white opaque plastic LDPE bottles with white droppers, with gray high density polyethylene (HDPE) caps as follows:

3mL in 5 mL bottle NDC70512-790-03
5 mL in 10 mL bottle NDC70512-790-05
10 mL in 10 mL bottle NDC70512-790-10

Storage: Store at 20° to 25°C (68° to 77°F). [See USP Controlled Room Temperature]. Protect from light.

17 PATIENT COUNSELING INFORMATION

17.1 Slow or Delayed Healing

Patients should be informed of the possibility that slow or delayed healing may occur while using nonsteroidal anti-inflammatory drugs (NSAIDs).

17.2 Avoiding Contamination of the Product

Patients should be instructed to avoid allowing the tip of the bottle to contact the eye or surrounding structures because this could cause the tip to become contaminated by common bacteria known to cause ocular infections. Serious damage to the eye and subsequent loss of vision may result from using contaminated solutions.

Also, to avoid the potential for cross-contamination, the patient should be advised to use one bottle for each eye following bilateral ocular surgery. The use of the same bottle of topical eye drops for both eyes following bilateral ocular surgery is not recommended.

17.3 Contact Lens Wear

Patients should be advised that ketorolac tromethamine ophthalmic solution should not be administered while wearing contact lenses.

17.4 Intercurrent Ocular Conditions

Patients should be advised that if they develop an intercurrent ocular condition (e.g., trauma or infection) or have ocular surgery, they should immediately seek their physician’s advice concerning the continued use of ketorolac tromethamine ophthalmic solution.

17.5 Concomitant Topical Ocular Therapy

Patients should be advised that if more than one topical ophthalmic medication is being used, the medicines should be administered at least 5 minutes apart.

Manufactured for:
SOLA Pharmaceuticals
Baton Rouge, LA 70810
Made in India

Code: TN/Drugs/TN00003457
Revised: 03/2024
22200826

Principal Display Panel Text for 3mL Container Label:

NDC 70512-790-03
Ketrolac Tromethamine
Ophthalmic Solution
0.5%
FOR TOPICAL OPHTHALMIC USE ONLY
Sterile
Rx only 3 mL
Each mL contains: 2200820
Active: ketorolac tromethamine 0.5%.
Preservative:benzalkonlum chloride 0.01%
Usual Dosage:One drop four times a day. Refer to
package insert.
Storage: Store at 20° - 25°C (68° - 77°F) [See USP
Controlled Room Temperature]. Protect from light.
Manufactured for:
SOLA Pharmaceuticals
Baton Rouge, LA 70810
Made in India
LOT:
EXP:
Code No.:TN/Drugs/TN00003457

Principal Display Panel Text for 3mL Carton Label:

NDC 70512-790-03

Ketorolac
Tromethamine
Opthalmic
Solution
0.5%

FOR TOPICAL
OPHTHALMIC USE ONLY
Sterile
Rx Only 3mL

Each mL contains:
Active: ketorolac tromethamine 0.5%.
Preservative: benzalkonlum chloride 0.01%
Inactives:edetate disodium
0.1%; octoxynol 40; water for
injection; sodium chloride; and
hydrochloric acid and/or sodium
hydroxide to adjust pH to 7.4.
Usual Dosage: One drop four times a day. Refer to
package insert.
Storage: Store at 20° - 25°C (68° - 77°F)
[See USP Controlled Room
Temperature].
Protect from light.
KEEP OUT OF REACH OF
CHILDREN
22200823
Manufactured for:
SOLA Pharmaceuticals
Baton Rouge, LA 70810
Made in India
Code No.:TN/Drugs/TN00003457

Principal Display Panel Text for 5mL Container Label:

NDC 70512-790-05
Ketrolac Tromethamine
Ophthalmic Solution
0.5%
FOR TOPICAL OPHTHALMIC USE ONLY
Sterile
Rx only 5 mL
Each mL contains: 2200831
Active: ketorolac tromethamine 0.5%.
Preservative:benzalkonlum chloride 0.01%
Usual Dosage:One drop four times a day. Refer to
package insert.
Storage: Store at 20° - 25°C (68° - 77°F) [See USP
Controlled Room Temperature]. Protect from light.
Note:Bottle filled to 1/2 capacity.
Manufactured for:
SOLA Pharmaceuticals
Baton Rouge, LA 70810
Made in India
LOT:
EXP:
Code No.:TN/Drugs/TN00003457

Principal Display Panel Text for 5mL Carton Label:

NDC 70512-790-05

Ketorolac
Tromethamine
Opthalmic
Solution
0.5%

FOR TOPICAL
OPHTHALMIC USE ONLY
Sterile
Rx Only 5 mL

Each mL contains:
Active: ketorolac tromethamine 0.5%.
Preservative: benzalkonlum chloride 0.01%
Inactives:edetate disodium
0.1%; octoxynol 40; water for
injection; sodium chloride; and
hydrochloric acid and/or sodium
hydroxide to adjust pH to 7.4.
Usual Dosage: One drop four times a day. Refer to
package insert.
Storage: Store at 20° - 25°C (68° - 77°F)
[See USP Controlled Room
Temperature].
Protect from light.
KEEP OUT OF REACH OF
CHILDREN
Note:Bottle filled to 1/2 capacity.
22200833
Manufactured for:
SOLA Pharmaceuticals
Baton Rouge, LA 70810
Made in India
Code No.:TN/Drugs/TN00003457

Principal Display Panel Text for 10mL Container Label:

NDC 70512-790-10
Ketrolac Tromethamine
Ophthalmic Solution
0.5%
FOR TOPICAL OPHTHALMIC USE ONLY
Sterile
Rx only 10 mL
Each mL contains: 2200832
Active: ketorolac tromethamine 0.5%.
Preservative:benzalkonlum chloride 0.01%
Usual Dosage:One drop four times a day. Refer to
package insert.
Storage: Store at 20° - 25°C (68° - 77°F) [See USP
Controlled Room Temperature]. Protect from light.
Manufactured for:
SOLA Pharmaceuticals
Baton Rouge, LA 70810
Made in India
LOT:
EXP:
Code No.:TN/Drugs/TN00003457

Principal Display Panel Text for 10mL Carton Label:

NDC 70512-790-10

Ketorolac
Tromethamine
Opthalmic
Solution
0.5%

FOR TOPICAL
OPHTHALMIC USE ONLY
Sterile
Rx Only 10 mL

Each mL contains:
Active: ketorolac tromethamine 0.5%.
Preservative: benzalkonlum chloride 0.01%
Inactives:edetate disodium
0.1%; octoxynol 40; water for
injection; sodium chloride; and
hydrochloric acid and/or sodium
hydroxide to adjust pH to 7.4.
Usual Dosage: One drop four times a day. Refer to
package insert.
Storage: Store at 20° - 25°C (68° - 77°F)
[See USP Controlled Room
Temperature].
Protect from light.
KEEP OUT OF REACH OF
CHILDREN
22200834
Manufactured for:
SOLA Pharmaceuticals
Baton Rouge, LA 70810
Made in India
Code No.:TN/Drugs/TN00003457